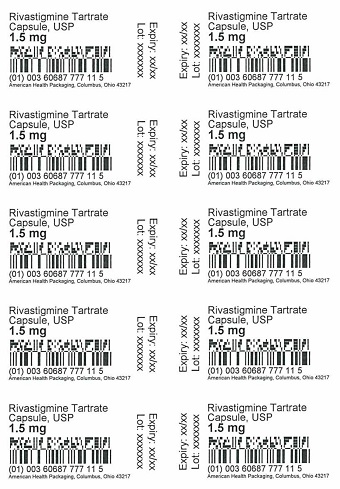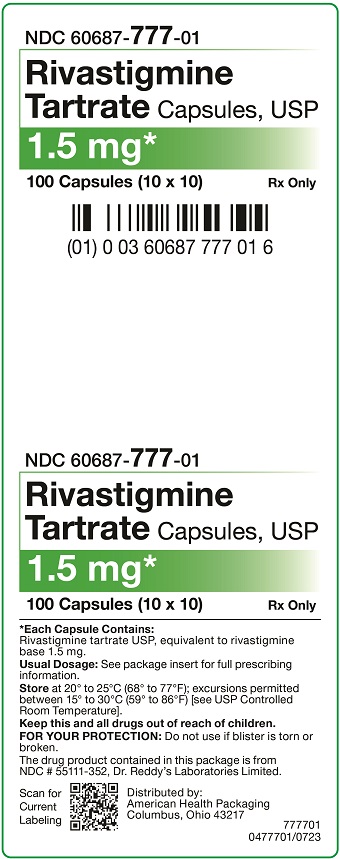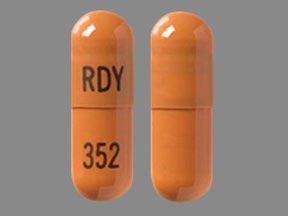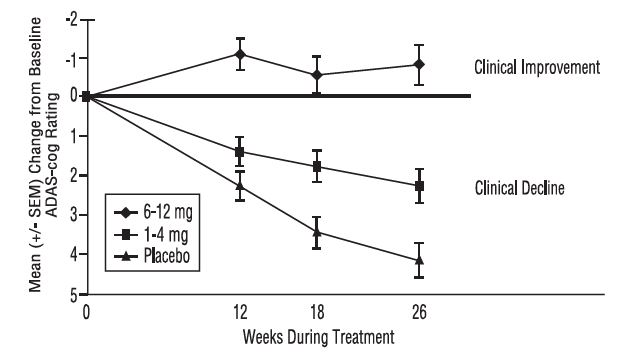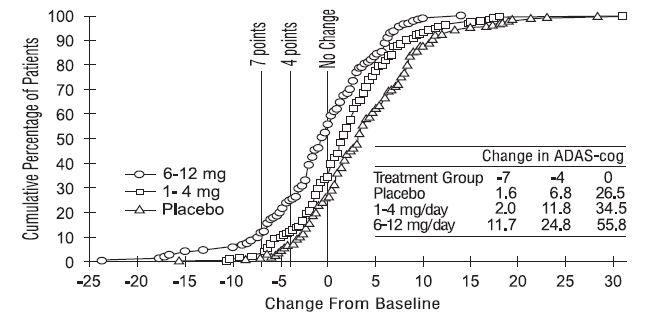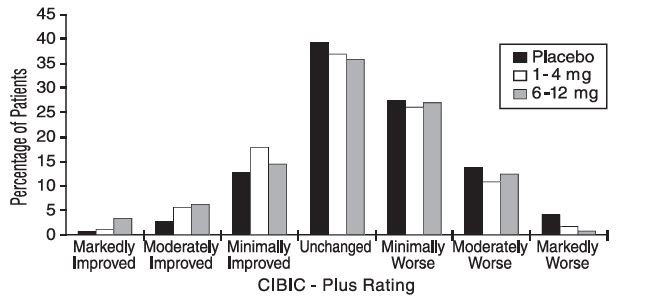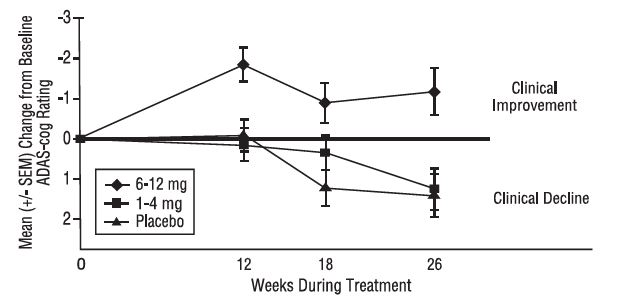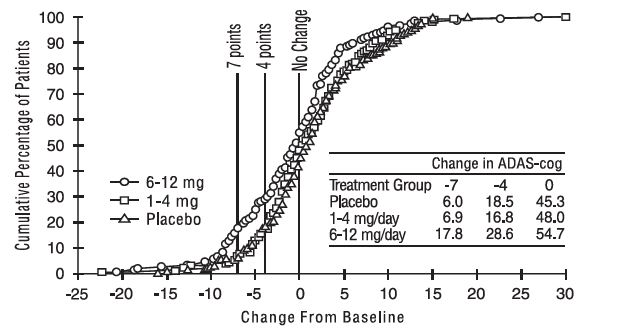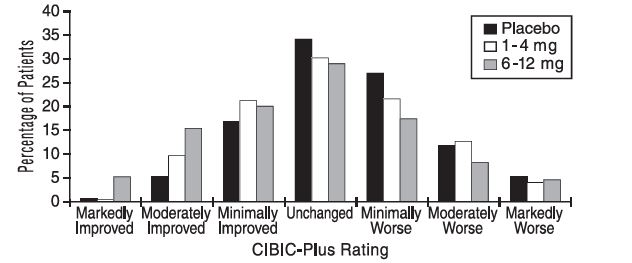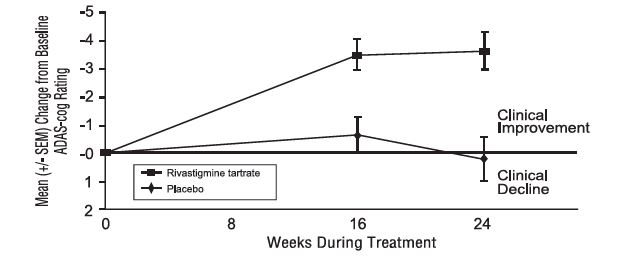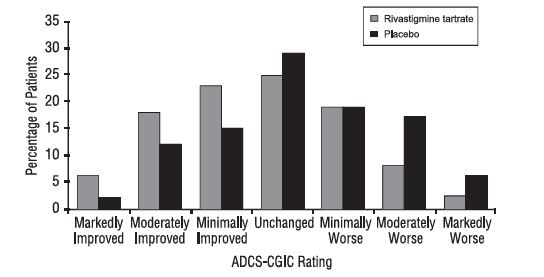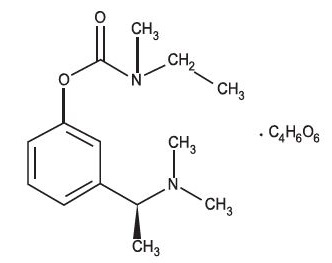 DRUG LABEL: Rivastigmine Tartrate
NDC: 60687-777 | Form: CAPSULE
Manufacturer: American Health Packaging
Category: prescription | Type: HUMAN PRESCRIPTION DRUG LABEL
Date: 20251111

ACTIVE INGREDIENTS: RIVASTIGMINE TARTRATE 1.5 mg/1 1
INACTIVE INGREDIENTS: SILICON DIOXIDE; HYPROMELLOSE 2910 (5 MPA.S); MAGNESIUM STEARATE; MICROCRYSTALLINE CELLULOSE; GELATIN, UNSPECIFIED; TITANIUM DIOXIDE; FERROSOFERRIC OXIDE; FERRIC OXIDE RED; FERRIC OXIDE YELLOW

HIGHLIGHTS OF PRESCRIBING INFORMATION

These highlights do not include all the information needed to use RIVASTIGMINE TARTRATE CAPSULES safely and effectively. See full prescribing information for RIVASTIGMINE TARTRATE CAPSULES.
RIVASTIGMINE TARTRATE capsules, for oral use
Initial U.S. Approval: 2000

1 INDICATIONS AND USAGE

Rivastigmine tartrate capsule is an acetylcholinesterase inhibitor indicated for treatment of:

- Mild-to-moderate dementia of the Alzheimer’s type (AD) (1.1)
- Mild-to-moderate dementia associated with Parkinson’s disease (PD) (1.2)

2 DOSAGE AND ADMINISTRATION

Alzheimer’s Disease (2.1):

- Initial Dose: Initiate treatment with 1.5 mg twice a day.
- Dose Titration: After a minimum of 2 weeks, if tolerated, increase dose to 3 mg twice a day and further to 4.5 mg twice a day and 6 mg twice a day if tolerated with a minimum of 2 weeks at each dose.

Parkinson’s Disease Dementia (PDD) (2.2):

- Initial Dose: Initiate treatment with 1.5 mg twice a day.
- Dose Titration: After a minimum of 4 weeks, if tolerated, increase dose to 3 mg twice a day and further to 4.5 mg twice a day and 6 mg twice a day if tolerated with a minimum of 4 weeks at each dose.

Rivastigmine tartrate capsule should be taken with meals in divided doses in the morning and evening (2.1, 2.2).

3 DOSAGE FORMS AND STRENGTHS

Capsules: 1.5 mg, 3 mg, 4.5 mg, or 6 mg (3.1)

4 CONTRAINDICATIONS

- Known hypersensitivity to rivastigmine, other carbamate derivatives or other components of the formulation. (4)
- History of application site reaction with rivastigmine transdermal patch suggestive of allergic contact dermatitis, in the absence of negative allergy testing. (4, 5.2)

5 WARNINGS AND PRECAUTIONS

- Gastrointestinal adverse reactions may include significant nausea, vomiting, diarrhea, anorexia/decreased appetite, and weight loss, and may necessitate treatment interruption. Dehydration may result from prolonged vomiting or diarrhea and can be associated with serious outcomes. (5.1)
- Discontinue rivastigmine in case of disseminated allergic dermatitis, which may occur after oral or transdermal administration (4, 5.2). In patients with suspected allergic contact dermatitis after transdermal rivastigmine use, switch to oral rivastigmine only after negative allergy testing.

6 ADVERSE REACTIONS

Most common adverse reactions (greater than 5% and 2 times greater than placebo): nausea, vomiting, anorexia, dyspepsia, and asthenia. (6.1)

To report SUSPECTED ADVERSE REACTIONS, contact Dr. Reddy’s Laboratories Inc., at 1-888-375-3784 or FDA at 1-800-FDA-1088 or www.fda.gov/medwatch.

7 DRUG INTERACTIONS

Concomitant use with metoclopramide, beta-blockers, or cholinomimetic and anticholinergic drugs is not recommended (7.1, 7.2, 7.3)

FULL PRESCRIBING INFORMATION

1 INDICATIONS AND USAGE

1.1 Alzheimer’s Disease

Rivastigmine tartrate capsules are indicated for the treatment of mild-to-moderate dementia of the Alzheimer's type (AD).

1.2 Parkinson’s Disease Dementia

Rivastigmine tartrate capsules are indicated for the treatment of mild-to-moderate dementia associated with Parkinson’s disease (PD).

2 DOSAGE AND ADMINISTRATION

2.1 Dosing in Alzheimer’s Disease

Rivastigmine tartrate capsules should be taken with meals in divided doses in the morning and evening.

The recommended dosage of rivastigmine tartrate capsules in Alzheimer’s disease (AD) is 6 mg to 12 mg per day, administered twice a day (daily doses of 3 mg to 6 mg twice a day). There is evidence from the clinical trials that doses at the higher end of this range may be more beneficial.

Initial Dose
Initiate treatment with the 1.5 mg twice a day with rivastigmine tartrate capsules.

Dose Titration
After a minimum of 2 weeks and if well tolerated, increase the dose to 3 mg twice a day. Subsequent increases to 4.5 mg twice a day and 6 mg twice a day should be attempted after a minimum of 2 weeks at the previous dose and if well tolerated. The maximum dose is 6 mg twice a day (12 mg per day).

2.2 Dosing in Parkinson’s Disease Dementia

Rivastigmine tartrate capsules should be taken with meals in divided doses in the morning and evening.

The dosage of rivastigmine tartrate capsules shown to be effective in the single controlled clinical trial conducted in dementia associated with Parkinson’s disease is 3 mg to 12 mg per day, administered twice a day (daily doses of 1.5 mg to 6 mg twice a day).

Initial Dose
Initiate treatment with the 1.5 mg twice a day with rivastigmine tartrate capsules.

Dose Titration
After a minimum of 4 weeks and if well tolerated, increase the dose to 3 mg twice a day. Subsequent increases to 4.5 mg twice a day and 6 mg twice a day should be attempted after a minimum of 4 weeks at the previous dose and if well tolerated. The maximum dose is 6 mg twice a day (12 mg per day).

2.3 Interruption of Treatment

If adverse effects (e.g., nausea, vomiting, abdominal pain, loss of appetite) cause intolerance during treatment, the patient should be instructed to discontinue treatment for several doses and then restart at the same or next lower dose level.

If dosing is interrupted for 3 days or fewer, restart treatment with the same or lower dose of rivastigmine tartrate capsules. If dosing is interrupted for more than 3 days, treatment should be restarted with 1.5 mg twice a day and titrated as described above [see Warnings and Precautions (5.1)].

2.4 Dosing in Specific Populations

Dosing Modifications in Patients with Renal Impairment
Patients with moderate and severe renal impairment may be able to only tolerate lower doses.

Dosing Modifications in Patients with Hepatic Impairment
Patients with mild (Child-Pugh score 5 to 6) and moderate (Child-Pugh score 7 to 9) hepatic impairment may be able to only tolerate lower doses. No data are available on the use of rivastigmine in patients with severe hepatic impairment.

Dosing Modifications in Patients with Low Body Weight
Carefully titrate and monitor patients with low body weight (less than 50 kg) for toxicities (e.g., excessive nausea, vomiting), and consider reducing the dose if such toxicities develop.

3 DOSAGE FORMS AND STRENGTHS

3.1 Rivastigmine Tartrate Capsules

Capsules, containing rivastigmine tartrate equivalent to 1.5 mg, 3 mg, 4.5 mg, or 6 mg of rivastigmine base, are available as follows:

Rivastigmine tartrate capsules USP, 1.5 mg are white to off-white powder filled in size ‘2’ hard gelatin capsules with light tan opaque color cap and light tan opaque color body, imprinted ‘RDY” on cap and ‘352’ on body with black ink.

Rivastigmine tartrate capsules USP, 3 mg are white to off-white powder filled in size ‘2’ hard gelatin capsules with brown opaque color cap and brown opaque color body, imprinted ‘RDY’ on cap and ‘353’ on body with black ink.

Rivastigmine tartrate capsules USP, 4.5 mg are white to off-white powder filled in size ‘2’ hard gelatin capsules with swedish orange opaque color cap and swedish orange opaque color body, imprinted 'RDY' on cap and '354' on body with black ink.

Rivastigmine tartrate capsules USP, 6 mg are white to off-white powder filled in size ‘2’ hard gelatin capsules with swedish orange opaque color cap and brown opaque color body, imprinted ‘RDY’ on cap and ‘355’ on body with black ink.

4 CONTRAINDICATIONS

Rivastigmine tartrate is contraindicated in patients with:

- known hypersensitivity to rivastigmine, other carbamate derivatives or other components of the formulation [see Description (11)]
- a previous history of application site reaction with rivastigmine transdermal patch suggestive of allergic contact dermatitis, in the absence of negative allergy testing [see Warnings and Precautions (5.2)]

Isolated cases of generalized skin reactions have been described in postmarketing experience [see Adverse Reactions (6.2)].

5 WARNINGS AND PRECAUTIONS

5.1 Gastrointestinal Adverse Reactions

Rivastigmine tartrate can cause gastrointestinal adverse reactions, including significant nausea, vomiting, diarrhea, anorexia/decreased appetite, and weight loss. Dehydration may result from prolonged vomiting or diarrhea and can be associated with serious outcomes. The incidence and severity of these reactions are dose-related [see Adverse Reactions (6.1)]. For this reason, patients should always be started at a dose of 1.5 mg twice a day and titrated to their maintenance dose.

If treatment is interrupted for longer than 3 days, treatment should be reinitiated with the lowest daily dose [see Dosage and Administration (2.3)] to reduce the possibility of severe vomiting and its potentially serious sequelae (e.g., there has been one postmarketing report of severe vomiting with esophageal rupture following inappropriate reinitiation of treatment with a 4.5 mg dose after 8 weeks of treatment interruption).

Inform caregivers to monitor for gastrointestinal adverse reactions and to inform the physician if they occur. It is critical to inform caregivers that if therapy has been interrupted for more than 3 days because of intolerance, the next dose should not be administered without contacting the physician regarding proper retitration.

5.2 Allergic Dermatitis

There have been isolated postmarketing reports of patients experiencing disseminated allergic dermatitis when administered rivastigmine irrespective of the route of administration (oral or transdermal). Treatment should be discontinued if disseminated allergic dermatitis occurs [see Contraindications (4)]. Patients and caregivers should be instructed accordingly [see Patient Counseling Information (17)].

In patients who develop application site reactions, suggestive of allergic contact dermatitis to rivastigmine tartrate patch and who still require rivastigmine, treatment should be switched to oral rivastigmine only after negative allergy testing and under close medical supervision. It is possible that some patients sensitized to rivastigmine by exposure to rivastigmine patch may not be able to take rivastigmine in any form.

5.3 Other Adverse Reactions from Increased Cholinergic Activity

Neurologic Effects
Extrapyramidal Symptoms: Cholinomimetics, including rivastigmine may exacerbate or induce extrapyramidal symptoms. Worsening of parkinsonian symptoms, particularly tremor has been observed in patients with dementia associated with Parkinson’s disease who were treated with rivastigmine tartrate capsules.

Seizures: Drugs that increase cholinergic activity are believed to have some potential for causing seizures. However, seizure activity also may be a manifestation of Alzheimer's disease.

Peptic Ulcers/Gastrointestinal Bleeding
Cholinesterase inhibitors, including rivastigmine, may be expected to increase gastric acid secretion due to increased cholinergic activity. Monitor patients using rivastigmine tartrate for symptoms of active or occult gastrointestinal bleeding, especially those at increased risk for developing ulcers, e.g., those with a history of ulcer disease or those receiving concurrent nonsteroidal anti-inflammatory drugs (NSAIDs). Clinical studies of rivastigmine have shown no significant increase, relative to placebo, in the incidence of either peptic ulcer disease or gastrointestinal bleeding.

Use with Anesthesia
Rivastigmine, as a cholinesterase inhibitor, is likely to exaggerate succinylcholine-type muscle relaxation during anesthesia.

Cardiac Conduction Effects
Because rivastigmine increases cholinergic activity, use of rivastigmine may have vagotonic effects on heart rate (e.g., bradycardia). The potential for this action may be particularly important in patients with sick sinus syndrome or other supraventricular cardiac conduction conditions. In clinical trials, rivastigmine was not associated with any increased incidence of cardiovascular adverse events, heart rate or blood pressure changes, or electrocardiogram (ECG) abnormalities. Syncopal episodes have been reported in 3% of patients receiving 6 mg to 12 mg per day of rivastigmine tartrate, compared to 2% of placebo patients.

Genitourinary Effects
Although not observed in clinical trials of rivastigmine, drugs that increase cholinergic activity may cause urinary obstruction.

Pulmonary Effects
Drugs that increase cholinergic activity, including rivastigmine, should be used with care in patients with a history of asthma or obstructive pulmonary disease.

5.4 Impairment in Driving or Use of Machinery

Dementia may cause gradual impairment of driving performance or compromise the ability to use machinery. The administration of rivastigmine may also result in adverse reactions that are detrimental to these functions. During treatment with the rivastigmine tartrate, routinely evaluate the patient’s ability to continue driving or operating machinery.

6 ADVERSE REACTIONS

The following adverse reactions are described below and elsewhere in the labeling:

- Gastrointestinal Adverse Reactions [see Warnings and Precautions (5.1)]
- Allergic Dermatitis [see Warnings and Precautions (5.2)]
- Other Adverse Reactions from Increased Cholinergic Activity [see Warnings and Precautions (5.3)]

6.1 Clinical Trials Experience

Because clinical trials are conducted under widely varying conditions, adverse reaction rates observed in the clinical trials of a drug cannot be directly compared to rates in the clinical trials of another drug and may not reflect the rates observed in practice.

Rivastigmine tartrate has been administered to over 5,297 individuals during clinical trials worldwide. Of these, 4,326 patients have been treated for at least 3 months, 3,407 patients have been treated for at least 6 months, 2,150 patients have been treated for 1 year, 1,250 patients have been treated for 2 years, and 168 patients have been treated for over 3 years. With regard to exposure to the highest dose, 2,809 patients were exposed to doses of 10 mg to 12 mg, 2,615 patients treated for 3 months, 2,328 patients treated for 6 months, 1,378 patients treated for 1 year, 917 patients treated for 2 years, and 129 patients treated for over 3 years.

Mild-to-Moderate Alzheimer’s Disease
Most Common Adverse Reactions
The most common adverse reactions, defined as those occurring at a frequency of at least 5% and twice the placebo rate, are largely predicted by rivastigmine tartrate's cholinergic effects. These include nausea, vomiting, anorexia, dyspepsia, and asthenia.

Gastrointestinal Adverse Reactions
Rivastigmine tartrate use is associated with significant nausea, vomiting, and weight loss [see Warnings and Precautions (5.1)].

Discontinuation Rates
The rate of discontinuation due to adverse events in controlled clinical trials of rivastigmine tartrate was 15% for patients receiving 6 mg to 12 mg per day compared to 5% for patients on placebo during forced weekly dose titration. While on a maintenance dose, the rates were 6% for patients on rivastigmine tartrate compared to 4% for those on placebo.

The most common adverse reactions leading to discontinuation, defined as those occurring in at least 2% of patients and at twice the incidence seen in placebo patients, are shown in Table 1.

Table 1 Most Frequent Adverse Reactions Leading to Withdrawal from Clinical Trials During Titration and Maintenance in Patients Receiving 6 mg to 12 mg per day Rivastigmine Tartrate Using a Forced-Dose Titration
Study Phase | Titration |  | Maintenance |  | Overall
 | Rivastigmine Tartrate; ≥ 6 to 12mg/day; (n=1,189) | Placebo; (n=868) | Rivastigmine Tartrate; ≥6 to 12mg/day; (n=987) | Placebo; (n=788) | Rivastigmine Tartrate; ≥6 to 12 mg/day; (n=1,189) | Placebo; (n=868)
Event/% Discontinuing
Nausea | 8 | <1 | 1 | <1 | 8 | 1
Vomiting | 4 | <1 | 1 | <1 | 5 | <1
Anorexia | 2 | 0 | 1 | <1 | 3 | <1
Dizziness | 2 | <1 | 1 | <1 | 2 | <1

Adverse Reactions Observed at an Incidence of at Least 2%
Table 2 lists adverse reactions that occurred in at least 2% of patients in placebo-controlled trials, and for which the rate of occurrence was greater for patients treated with rivastigmine tartrate doses of 6 mg to 12 mg per day than for those treated with placebo.

In general, adverse reactions were less frequent later in the course of treatment.

No systematic effect of race or age could be determined from the incidence of adverse reactions in the controlled studies. Nausea, vomiting and weight loss were more frequent in women than men.

Table 2 Proportion of Adverse Reactions Observed with a Frequency of Greater Than or Equal to 2% and at a Rate Greater than Placebo in Clinical Trials
Body System/Adverse Reaction | Rivastigmine Tartrate; (6 to 12 mg/day); (n=1,189) | Placebo; (n=868)
Percent of Patients with any Adverse Event | 92 | 79
Autonomic Nervous System
Increased Sweating | 4 | 1
Syncope | 3 | 2
Body as a Whole
Fatigue | 9 | 5
Asthenia | 6 | 2
Malaise | 5 | 2
Decreased Weight** | 3 | <1
Cardiovascular Disorders, General
Hypertension | 3 | 2
Central and Peripheral Nervous System
Dizziness | 21 | 11
Headache | 17 | 12
Somnolence | 5 | 3
Tremor | 4 | 1
Gastrointestinal System
Nausea* | 47 | 12
Vomiting* | 31 | 6
Diarrhea | 19 | 11
Anorexia*** | 17 | 3
Abdominal Pain | 13 | 6
Dyspepsia | 9 | 4
Psychiatric Disorders
Insomnia | 9 | 7
Confusion | 8 | 7
Depression | 6 | 4
Anxiety | 5 | 3
Hallucination | 4 | 3
Aggressive Reaction | 3 | 2
Resistance Mechanism Disorders
Urinary Tract Infection | 7 | 6

*Nausea and Vomiting: In the controlled clinical trials, 47% of the patients treated with rivastigmine tartrate dose in the therapeutic range of 6 mg to 12 mg per day (n=1189) developed nausea (compared with 12% in placebo). A total of 31% of rivastigmine tartrate-treated patients developed at least 1 episode of vomiting (compared with 6% for placebo). The rate of vomiting was higher during the titration phase (24% versus 3% for placebo) than in the maintenance phase (14% versus 3% for placebo). The rates were higher in women than men. Five percent of patients discontinued for vomiting, compared to less than 1% for patients on placebo. Vomiting was severe in 2% of rivastigmine tartrate-treated patients and was rated as mild or moderate each in 14% of patients. The rate of nausea was higher during the titration phase (43% versus 9% for placebo) than in the maintenance phase (17% versus 4% for placebo).

**Weight Decreased: In the controlled trials, approximately 26% of women on high doses of rivastigmine tartrate (greater than 9 mg per day) had weight loss equal to or greater than 7% of their baseline weight compared to 6% in the placebo-treated patients. About 18% of the males in the high-dose group experienced a similar degree of weight loss compared to 4% in placebo-treated patients. It is not clear how much of the weight loss was associated with anorexia, nausea, vomiting, and the diarrhea associated with the drug.

***Anorexia: In the controlled clinical trials, of the patients treated with rivastigmine tartrate dose of 6 mg to 12 mg per day, 17% developed anorexia compared to 3% of the placebo patients. Neither the time course nor the severity of the anorexia is known.

Mild-to-Moderate Parkinson’s Disease Dementia
Rivastigmine tartrate has been administered to 779 individuals during clinical trials worldwide. Of these, 663 patients have been treated for at least 3 months, 476 patients have been treated for at least 6 months, and 313 patients have been treated for 1 year.=

Most Common Adverse Reactions
The most common adverse reactions, defined as those occurring at a frequency of at least 5% and twice the placebo rate, are largely predicted by rivastigmine tartrate's cholinergic effects. These include nausea, vomiting, tremor, anorexia, and dizziness.

Discontinuation Rates
The rate of discontinuation due to adverse events in the single placebo-controlled trial of rivastigmine tartrate was 18% for patients receiving 3 mg to 12 mg per day compared to 11% for patients on placebo during the 24 week study.

The most frequent adverse reactions that led to discontinuation from this study, defined as those occurring in at least 1% of patients receiving rivastigmine tartrate and more frequent than those receiving placebo, were nausea (3.6% rivastigmine tartrate versus 0.6% placebo), vomiting (1.9% rivastigmine tartrate versus 0.6% placebo), and tremor (1.7% rivastigmine tartrate versus 0% placebo).

Adverse Reactions Observed at an Incidence of at Least 2%
Table 3 lists adverse reactions that occurred in at least 2% of patients in a single placebo-controlled trial and during the first 24 weeks of a 76 week open-label active-controlled trial for which the rate of occurrence was greater for patients treated with rivastigmine tartrate doses of 3 mg to 12 mg per day than for those treated with placebo in the placebo-controlled trial.

In general, adverse reactions were less frequent later in the course of treatment.

Table 3 Proportion of Adverse Reactions Observed at a Frequency Greater Than or Equal to 2% and Occurring at Rate Greater than Placebo in Clinical Trials
 | Active-Controlled Study | Placebo-Controlled Study
Body System/Adverse Reaction | Rivastigmine Tartrate; (3 to 12 mg/day); (n=294) | Rivastigmine Tartrate; (3 to 12 mg/day); (n=362) | Placebo; (n=179)
Percent of Patients with any Adverse Event | 88 | 84 | 71
Gastrointestinal Disorders
Nausea | 38 | 29 | 11
Vomiting | 13 | 17 | 2
Diarrhea | 8 | 7 | 4
Upper Abdominal Pain | 4 | 4 | 1
Salivary hypersecretion | 2 | 1 | 0
General Disorders and Administrative Site Conditions
Fall | 10 | 6 | 6
Fatigue | 5 | 4 | 3
Asthenia | 4 | 2 | 1
Metabolism and Nutritional Disorders
Anorexia | - | 6 | 3
Decreased Appetite | 5 | 8 | 5
Dehydration | 1 | 2 | 1
Nervous System Disorders
Tremor | 23 | 10 | 4
Dizziness | 8 | 6 | 1
Headache | 4 | 4 | 3
Somnolence | 6 | 4 | 3
Parkinson's Disease (worsening) | -* | 3 | 1
Bradykinesia | 3 | 3 | 2
Dyskinesia | 3 | 1 | 1
Cogwheel rigidity | 3 | 1 | 0
Hypokinesia | 2 | 1 | 0
Parkinsonism | - | 2 | 1
Psychiatric Disorders
Anxiety | 4 | 4 | 1
Insomnia | 2 | 3 | 2
Restlessness | 1 | 3 | 2
Skin and Subcutaneous Tissue Disorders
Increased Sweating | 2 | 2 | 1

*Parkinson’s disease (worsening) in the active-controlled study was assessed by reported pre-identified adverse events (tremor, cogwheel rigidity, fall), each of them listed with corresponding frequencies.

6.2 Postmarketing Experience

The following adverse reactions have been identified during post approval use of rivastigmine tartrate capsules. Because these reactions are reported voluntarily from a population of uncertain size, it is not always possible to reliably estimate their frequency or establish a causal relationship to drug exposure.

Cardiac Disorders: Tachycardia.

Hepatobiliary Disorders: Abnormal liver function tests, hepatitis

Nervous System Disorders: seizure

Psychiatric Disorders: Aggression, nightmares

Skin and Subcutaneous Tissue Disorders: Allergic dermatitis, application site hypersensitivity (patch), blister, disseminated allergic dermatitis, Stevens-Johnson syndrome, urticaria

7 DRUG INTERACTIONS

7.1 Metoclopramide

Due to the risk of additive extrapyramidal adverse reactions, the concomitant use of metoclopramide and rivastigmine tartrate is not recommended.

7.2 Cholinomimetic and Anticholinergic Medications

Rivastigmine tartrate may increase the cholinergic effects of other cholinomimetic medications and may also interfere with the activity of anticholinergic medications (e.g., oxybutynin, tolterodine). Concomitant use of rivastigmine tartrate with medications having these pharmacologic effects is not recommended unless deemed clinically necessary [see Warnings and Precautions (5.3)].

7.3 Beta-blockers

Additive bradycardic effects resulting in syncope may occur when rivastigmine tartrate is used concomitantly with beta-blockers, especially cardioselective beta-blockers (including atenolol). Concomitant use of rivastigmine tartrate with beta-blockers is not recommended.

8 USE IN SPECIFIC POPULATIONS

8.1 Pregnancy

Risk Summary
There are no adequate data on the developmental risks associated with the use of rivastigmine tartrate in pregnant women. In animals, no adverse effects on embryo-fetal development were observed at oral doses 2 to 4 times the maximum recommended human dose (MRHD) (see Data).

The background risk of major birth defects and miscarriage for the indicated population is unknown. In the U.S. general population, the estimated background risk of major birth defects and miscarriage in clinically recognized pregnancies is 2% to 4% and 15% to 20%, respectively.

Data
Animal Data
Oral administration of rivastigmine to pregnant rats and rabbits throughout organogenesis produced no adverse effects on embryo-fetal development up to the highest dose tested (2.3 mg/kg/day), which is 2 and 4 times, respectively, the MRHD of 12 mg per day on a body surface area (mg/m^2) basis.

8.2 Lactation

Risk Summary
There are no data on the presence of rivastigmine in human milk, the effects on the breastfed infant, or the effects of rivastigmine on milk production. Rivastigmine and its metabolites are excreted in rat milk following oral administration of rivastigmine; levels of rivastigmine plus metabolites in rat milk are approximately 2 times that in maternal plasma.

The developmental and health benefits of breastfeeding should be considered along with the mother’s clinical need for rivastigmine tartrate and any potential adverse effects on the breastfed infant from rivastigmine tartrate or from the underlying maternal condition.

8.4 Pediatric Use

Safety and effectiveness in pediatric patients have not been established. The use of rivastigmine tartrate in pediatric patients (below 18 years of age) is not recommended.

8.5 Geriatric Use

Of the total number of patients in clinical studies of rivastigmine tartrate, 86% were 65 years and older while 46% were 75 years and older. No overall differences in safety or effectiveness were observed between these patients and younger patients, and other reported clinical experience has not identified differences in responses between the elderly and younger patients, but greater sensitivity of some older individuals cannot be ruled out.

8.6 Renal Impairment

Patients with moderate to severe renal impairment may be able to only tolerate lower doses [see Dosage and Administration (2.4), Clinical Pharmacology (12.3)].

8.7 Hepatic Impairment

Patients with mild or moderate hepatic impairment may be able to only tolerate lower doses [see Dosage and Administration (2.4), Clinical Pharmacology (12.3)]. No data are available on the use of rivastigmine tartrate in patients with severe hepatic impairment.

8.8 Low or High Body Weight

Because rivastigmine blood levels vary with weight, careful titration and monitoring should be performed in patients with low or high body weights [see Dosage and Administration (2.4), Clinical Pharmacology (12.3)].

10 OVERDOSAGE

Because strategies for the management of overdose are continually evolving, it is advisable to contact a Poison Control Center to determine the latest recommendations for the management of an overdose of any drug.

As rivastigmine has a short plasma half-life of about 1 hour and a moderate duration of acetylcholinesterase inhibition of 8 to 10 hours, it is recommended that in cases of asymptomatic overdoses, no further dose of rivastigmine tartrate should be administered for the next 24 hours.

As in any case of overdose, general supportive measures should be utilized.

Overdosage with cholinesterase inhibitors can result in cholinergic crisis characterized by severe nausea, vomiting, salivation, sweating, bradycardia, hypotension, respiratory depression, collapse and convulsions. Increasing muscle weakness is a possibility and may result in death if respiratory muscles are involved. Atypical responses in blood pressure and heart rate have been reported with other drugs that increase cholinergic activity when coadministered with quaternary anticholinergics such as glycopyrrolate. Additional symptoms associated with rivastigmine overdose are diarrhea, abdominal pain, dizziness, tremor, headache, somnolence, confusional state, hyperhidrosis, hypertension, hallucinations and malaise. Due to the short half-life of rivastigmine, dialysis (hemodialysis, peritoneal dialysis, or hemofiltration) would not be clinically indicated in the event of an overdose.

In overdoses accompanied by severe nausea and vomiting, the use of antiemetics should be considered. A fatal outcome has been rarely reported with rivastigmine.

11 DESCRIPTION

Rivastigmine tartrate USP is a reversible cholinesterase inhibitor and is known chemically as (S)-N-Ethyl-N-methyl-3-[1-(dimethylamino)ethyl]-phenyl carbamate hydrogen-(2R,3R)-tartrate. Rivastigmine tartrate is commonly referred to in the pharmacological literature as SDZ ENA 713 or ENA 713. It has a molecular formula of C14H22N2O2• C4H6O6 (hydrogen tartrate salt – hta salt) and a molecular weight of 400.43 g/mol (hta salt). Rivastigmine tartrate is a white to off-white powder, that is very soluble in water and in methanol, very slightly soluble in ethyl acetate and soluble in ethanol.

The distribution coefficient at 37°C in n-octanol/phosphate buffer solution pH 7 is 3.0.

Rivastigmine tartrate capsules, USP contain rivastigmine tartrate, equivalent to 1.5 mg, 3 mg, 4.5 mg and 6 mg of rivastigmine base for oral administration. Inactive ingredients are colloidal silicon dioxide, hypromellose 5 cps, magnesium Stearate and microcrystalline cellulose. Each hard-gelatin capsule contains gelatin, titanium dioxide and black, red and yellow iron oxides (1.5 mg), red and yellow iron oxides (3 mg and 6 mg) and red iron oxide (4.5 mg).

12 CLINICAL PHARMACOLOGY

12.1 Mechanism of Action

Although the precise mechanism of action of rivastigmine is unknown, it is thought to exert its therapeutic effect by enhancing cholinergic function. This is accomplished by increasing the concentration of acetylcholine through reversible inhibition of its hydrolysis by cholinesterase. Therefore, the effect of rivastigmine may lessen as the disease process advances and fewer cholinergic neurons remain functionally intact. There is no evidence that rivastigmine alters the course of the underlying dementing process.

12.2 Pharmacodynamics

After a 6 mg dose of rivastigmine, anticholinesterase activity is present in cerebrospinal fluid (CSF) for about 10 hours, with a maximum inhibition of about 60% 5 hours after dosing.

In vitro and in vivo studies demonstrate that the inhibition of cholinesterase by rivastigmine is not affected by the concomitant administration of memantine, an N-methyl-D-aspartate receptor antagonist.

12.3 Pharmacokinetics

Rivastigmine shows linear pharmacokinetics up to 3 mg twice a day but is nonlinear at higher doses. Doubling the dose from 3 mg to 6 mg twice a day results in a 3 fold increase in area under curve (AUC). The elimination half-life is about 1.5 hours, with most elimination as metabolites via the urine.

Absorption
Rivastigmine is rapidly and completely absorbed. Peak plasma concentrations are reached in approximately 1 hour. Absolute bioavailability after a 3 mg dose is about 36%. Administration of rivastigmine tartrate with food delays absorption (Tmax) by 90 minutes lowers Cmax by approximately 30% and increases AUC by approximately 30%.

Distribution
Rivastigmine is weakly bound to plasma proteins (approximately 40%) over the therapeutic range. It readily crosses the blood-brain barrier, reaching CSF peak concentrations in 1.4 to 2.6 hours. It has an apparent volume of distribution (VD) in the range of 1.8 to 2.7 L/kg.

Metabolism
Rivastigmine is rapidly and extensively metabolized, primarily via cholinesterase-mediated hydrolysis to the decarbamylated metabolite. Based on evidence from in vitro and animal studies, the major cytochrome P450 isozymes are minimally involved in rivastigmine metabolism. Consistent with these observations is the finding that no drug interactions related to cytochrome P450 have been observed in humans.

Elimination
The major pathway of elimination is via the kidneys. Following administration of^14C-rivastigmine to 6 healthy volunteers, total recovery of radioactivity over 120 hours was 97% in urine and 0.4% in feces. No parent drug was detected in urine. The sulfate conjugate of the decarbamylated metabolite is the major component excreted in urine and represents 40% of the dose. Mean oral clearance of rivastigmine is 1.8 ± 0.6 L/min after 6 mg twice a day.

Age
Following a single 2.5 mg oral dose to elderly volunteers (60 years and older, n=24) and younger volunteers (n=24), mean oral clearance of rivastigmine was 30% lower in elderly (7 L/min) than in younger subjects (10 L/min).

Gender and Race
Population pharmacokinetic analysis of oral rivastigmine indicated that neither gender (n=277 males and 348 females) nor race (n=575 Caucasian, 34 Black, 4 Asian, and 12 Other) affected clearance of the drug.

Body Weight
A relationship between drug exposure at steady-state (rivastigmine and metabolite NAP226-90) and body weight was observed in Alzheimer’s dementia patients. Rivastigmine exposure is higher in subjects with low body weight. Compared to a patient with a body weight of 65 kg, the rivastigmine steady-state concentrations in a patient with a body weight of 35 kg would be approximately doubled, while for a patient with a body weight of 100 kg the concentrations would be approximately halved.

Renal Impairment
Following a single 3 mg dose, mean oral clearance of rivastigmine is 64% lower in moderately impaired renal patients (n=8, GFR=10 to 50 mL/min) than in healthy subjects (n=10, GFR greater than or equal to 60 mL/min); CL/F=1.7 L/min and 4.8 L/min, respectively. In patients with severe renal impairment (n=8, GFR less than 10 mL/min), mean oral clearance of rivastigmine is 43% higher than in healthy subjects (n=10, GFR greater than or equal to 60 mL/min); CL/F=6.9 L/min and 4.8 L/min, respectively. For unexplained reasons, the severely impaired renal patients had a higher clearance of rivastigmine than moderately impaired patients.

Hepatic Impairment
Following a single 3 mg dose, mean oral clearance of rivastigmine was 60% lower in hepatically impaired patients (n=10, biopsy proven) than in healthy subjects (n=10). After multiple 6 mg twice a day oral dosing, the mean clearance of rivastigmine was 65% lower in mild (n=7, Child-Pugh score 5 to 6) and moderate (n=3, Child-Pugh score 7 to 9) hepatically impaired patients (biopsy proven, liver cirrhosis) than in healthy subjects (n=10).

Smoking
Following oral rivastigmine administration (up to 12 mg per day) with nicotine use, population pharmacokinetic analysis showed increased oral clearance of rivastigmine by 23% (n=75 smokers and 549 nonsmokers).

Drug Interaction Studies
Effect of Rivastigmine on the Metabolism of Other Drugs
Rivastigmine is primarily metabolized through hydrolysis by esterases. Minimal metabolism occurs via the major cytochrome P450 isoenzymes. Based on in vitro studies, no pharmacokinetic drug interactions with drugs metabolized by the following isoenzyme systems are expected: CYP1A2, CYP2D6, CYP3A4/5, CYP2E1, CYP2C9, CYP2C8, CYP2C19, or CYP2B6.

No pharmacokinetic interaction was observed between rivastigmine taken orally and digoxin, warfarin, diazepam or fluoxetine in studies in healthy volunteers. The increase in prothrombin time induced by warfarin is not affected by administration of rivastigmine.

Effect of Other Drugs on the Metabolism of Rivastigmine
Drugs that induce or inhibit CYP450 metabolism are not expected to alter the metabolism of rivastigmine.

Population pharmacokinetic analysis with a database of 625 patients showed that the pharmacokinetics of rivastigmine taken orally were not influenced by commonly prescribed medications such as antacids (n=77), antihypertensives (n=72), beta-blockers (n=42), calcium channel blockers (n=75), antidiabetics (n=21), NSAIDs (n=79), estrogens (n=70), salicylate analgesics (n=177), antianginals (n=35) and antihistamines (n=15).

13 NONCLINICAL TOXICOLOGY

13.1 Carcinogenesis, Mutagenesis, Impairment Of Fertility

Carcinogenesis
In oral carcinogenicity studies conducted at doses up to 1.1 mg/kg/day in rats and 1.6 mg/kg/day in mice, rivastigmine was not carcinogenic. These doses are less than the maximum recommended human dose (MRHD) of 12 mg per day on an mg/m^2 basis.

Mutagenesis
Rivastigmine was clastogenic in in vitro chromosomal aberration assays in mammalian cells in the presence, but not the absence, of metabolic activation. Rivastigmine was negative in an in vitro bacterial reverse mutation (Ames) assay, an in vitro HGPRT assay, and in an in vivo mouse micronucleus test.

Impairment of Fertility
Rivastigmine had no effect on fertility or reproductive performance in rats at oral doses up to 1.1 mg/kg/day, a dose less than the MRHD on an mg/m^2 basis.

14 CLINICAL STUDIES

Mild-to-Moderate Alzheimer’s Disease
The effectiveness of rivastigmine tartrate as a treatment for Alzheimer's disease is demonstrated by the results of 2 randomized, double-blind, placebo-controlled clinical investigations (Study 1 and Study 2) in patients with Alzheimer's disease [diagnosed by NINCDS-ADRDA and DSM-IV criteria, Mini-Mental State Examination (MMSE) greater than or equal to 10 and less than or equal to 26, and the Global Deterioration Scale (GDS)]. The mean age of patients participating in rivastigmine tartrate trials was 73 years with a range of 41 to 95. Approximately 59% of patients were women and 41% were men. The racial distribution was Caucasian 87%, Black 4%, and other races 9%.

In each study, the effectiveness of rivastigmine tartrate was evaluated using a dual outcome assessment strategy.

The ability of rivastigmine tartrate to improve cognitive performance was assessed with the cognitive subscale of the Alzheimer's Disease Assessment Scale (ADAS-cog), a multi-item instrument that has been extensively validated in longitudinal cohorts of Alzheimer's disease patients. The ADAS-cog examines selected aspects of cognitive performance including elements of memory, orientation, attention, reasoning, language, and praxis. The ADAS-cog scoring range is from 0 to 70, with higher scores indicating greater cognitive impairment. Elderly normal adults may score as low as 0 or 1, but it is not unusual for non-demented adults to score slightly higher.

The patients recruited as participants in each study had mean scores on ADAS-cog of approximately 23 units, with a range from 1 to 61. Experience gained in longitudinal studies of ambulatory patients with mild-to-moderate Alzheimer's disease suggests that they gain 6 to 12 units a year on the ADAS-cog. Lesser degrees of change, however, are seen in patients with very mild or very advanced disease because the ADAS-cog is not uniformly sensitive to change over the course of the disease. The annualized rate of decline in the placebo patients participating in rivastigmine tartrate trials was approximately 3 to 8 units per year.

The ability of rivastigmine tartrate to produce an overall clinical effect was assessed using a Clinician's Interview-Based Impression of Change (CIBIC) that required the use of caregiver information, the CIBIC-Plus. The CIBIC-Plus is not a single instrument and is not a standardized instrument like the ADAS-cog. Clinical trials for investigational drugs have used a variety of CIBIC formats, each different in terms of depth and structure. As such, results from a CIBIC-Plus reflect clinical experience from the trial or trials in which it was used and cannot be compared directly with the results of CIBIC-Plus evaluations from other clinical trials. The CIBIC-Plus used in the rivastigmine tartrate trials was a structured instrument based on a comprehensive evaluation at baseline and subsequent time-points of 3 domains: patient cognition, behavior and functioning, including assessment of activities of daily living. It represents the assessment of a skilled clinician using validated scales based on his/her observation at interviews conducted separately with the patient and the caregiver familiar with the behavior of the patient over the interval rated. The CIBIC-Plus is scored as a 7 point categorical rating, ranging from a score of 1, indicating "markedly improved," to a score of 4, indicating "no change" to a score of 7, indicating "marked worsening." The CIBIC-Plus has not been systematically compared directly to assessments not using information from caregivers or other global methods.

U.S. 26 Week Study of Rivastigmine Tartrate in Mild-to-Moderate Alzheimer’s Disease (Study 1)
In a study of 26 weeks duration, 699 patients were randomized to either a dose range of 1 mg to 4 mg or 6 mg to 12 mg of rivastigmine tartrate per day or to placebo, each given in divided doses. The 26 week study was divided into a 12 week forced-dose titration phase and a 14 week maintenance phase. The patients in the active treatment arms of the study were maintained at their highest tolerated dose within the respective range.

Figure 1 illustrates the time course for the change from baseline in ADAS-cog scores for all 3 dose groups over the 26 weeks of the study. At 26 weeks of treatment, the mean differences in the ADAS-cog change scores for the rivastigmine tartrate-treated patients compared to the patients on placebo were 1.9 and 4.9 units for the 1 mg to 4 mg and 6 mg to 12 mg treatments, respectively. Both treatments were statistically significantly superior to placebo and the 6 mg to 12 mg per day range was significantly superior to the 1 mg to 4 mg per day range.

Figure 1: Time-course of the Change from Baseline in ADAS-cog Score for Patients Completing 26 Weeks of Treatment in Study 1

Figure 2 illustrates the cumulative percentages of patients from each of the 3 treatment groups who had attained at least the measure of improvement in ADAS-cog score shown on the X-axis. Three change scores, (7 point and 4 point reductions from baseline or no change in score) have been identified for illustrative purposes, and the percent of patients in each group achieving that result is shown in the inset table.

The curves demonstrate that both patients assigned to rivastigmine tartrate and placebo have a wide range of responses, but that the rivastigmine tartrate groups are more likely to show the greater improvements. A curve for an effective treatment would be shifted to the left of the curve for placebo, while an ineffective or deleterious treatment would be superimposed upon, or shifted to the right of the curve for placebo, respectively.

Figure 2: Cumulative Percentage of Patients Completing 26 Weeks of Double-blind Treatment with Specified Changes from Baseline ADAS-cog Scores. The Percentages of Randomized Patients who Completed the Study were: Placebo 84%, 1 mg to 4 mg 85%, and 6 mg to 12 mg 65%.

Figure 3 is a histogram of the frequency distribution of CIBIC-Plus scores attained by patients assigned to each of the 3 treatment groups who completed 26 weeks of treatment. The mean rivastigmine tartrate-placebo differences for these groups of patients in the mean rating of change from baseline were 0.32 units and 0.35 units for 1 mg to 4 mg and 6 mg to 12 mg of Rivastigmine Tartrate, respectively. The mean ratings for the 6 mg to 12 mg per day and 1 mg to 4 mg per day groups were statistically significantly superior to placebo. The differences between the 6 mg to 12 mg per day and the 1 mg to 4 mg per day groups were statistically significant.

Figure 3: Frequency Distribution of CIBIC-Plus Scores at Week 26 in Study 1

Global 26 Week Study in Mild-to-Moderate Alzheimer’s Disease (Study 2)
In a second study of 26 weeks duration, 725 patients were randomized to either a dose range of 1 mg to 4 mg or 6 mg to 12 mg of rivastigmine tartrate per day or to placebo, each given in divided doses. The 26 week study was divided into a 12 week forced-dose titration phase and a 14 week maintenance phase. The patients in the active treatment arms of the study were maintained at their highest tolerated dose within the respective range.

Figure 4 illustrates the time course for the change from baseline in ADAS-cog scores for all 3 dose groups over the 26 weeks of the study. At 26 weeks of treatment, the mean differences in the ADAS-cog change scores for the rivastigmine tartrate-treated patients compared to the patients on placebo were 0.2 and 2.6 units for the 1 mg to 4 mg and 6 mg to 12 mg treatments, respectively. The 6 mg to 12 mg per day group was statistically significantly superior to placebo, as well as to the 1 mg to 4 mg per day group. The difference between the 1 mg to 4 mg per day group and placebo was not statistically significant.

Figure 4: Time-course of the Change from Baseline in ADAS-cog Score for Patients Completing 26 Weeks of Treatment

Figure 5 illustrates the cumulative percentages of patients from each of the 3 treatment groups who had attained at least the measure of improvement in ADAS-cog score shown on the X-axis. Similar to the U.S. 26 week study, the curves demonstrate that both patients assigned to rivastigmine tartrate and placebo have a wide range of responses, but that the 6 mg to 12 mg per day rivastigmine tartrate group is more likely to show the greater improvements.

Figure 5: Cumulative Percentage of Patients Completing 26 Weeks of Double-blind Treatment with Specified Changes from Baseline ADAS-cog Scores. The Percentages of Randomized Patients who Completed the Study were: Placebo 87%, 1 mg to 4 mg 86%, and 6 mg to 12 mg 67%.

Figure 6 is a histogram of the frequency distribution of CIBIC-Plus scores attained by patients assigned to each of the 3 treatment groups who completed 26 weeks of treatment. The mean rivastigmine tartrate-placebo differences for these groups of patients for the mean rating of change from baseline were 0.14 units and 0.41 units for 1 mg to 4 mg and 6 mg to 12 mg of rivastigmine tartrate, respectively. The mean ratings for the 6 mg to 12 mg per day group were statistically significantly superior to placebo. The comparison of the mean ratings for the 1 mg to 4 mg per day group and placebo group was not statistically significant.

Figure 6: Frequency Distribution of CIBIC-Plus Scores at Week 26 in Study 2

U.S. Fixed-Dose Study in Mild to Moderate Alzheimer’s Disease (Study 3)
In a study of 26 weeks duration, 702 patients were randomized to doses of 3 mg, 6 mg, or 9 mg per day of rivastigmine tartrate or to placebo, each given in divided doses. The fixed-dose study design, which included a 12 week forced-dose titration phase and a 14 week maintenance phase, led to a high dropout rate in the 9 mg per day group because of poor tolerability. At 26 weeks of treatment, significant differences were observed for the ADAS-cog mean change from baseline for the 9 mg per day and 6 mg per day groups, compared to placebo. No significant differences were observed between any of the rivastigmine tartrate-dose groups and placebo for the analysis of the CIBIC-Plus mean rating of change. Although no significant differences were observed between rivastigmine tartrate treatment groups, there was a trend toward numerical superiority with higher doses.

Mild-to-Moderate Parkinson’s Disease Dementia
International 24 Week Study (Study 4)
The effectiveness of rivastigmine tartrate as a treatment for dementia associated with Parkinson’s disease is demonstrated by the results of 1 randomized, double-blind, placebo-controlled clinical investigation in patients with mild-to-moderate dementia, with onset at least 2 years after the initial diagnosis of idiopathic Parkinson’s disease. The diagnosis of idiopathic Parkinson’s disease was based on the United Kingdom Parkinson’s Disease Society Brain Bank clinical criteria. The diagnosis of dementia was based on the criteria stipulated under the DSM-IV category “Dementia Due To Other General Medical Condition” (code 294.1x), but patients were not required to have a distinctive pattern of cognitive deficits as part of the dementia. Alternate causes of dementia were excluded by clinical history, physical and neurological examination, brain imaging, and relevant blood tests. Patients enrolled in the study had a MMSE score greater than or equal to 10 and less than or equal to 24 at entry. The mean age of patients participating in this trial was 72.7 years with a range of 50 to 91 years. Approximately, 35.1% of patients were women and 64.9% of patients were men. The racial distribution was 99.6% Caucasian and other races 0.4%.

This study used a dual outcome assessment strategy to evaluate the effectiveness of rivastigmine tartrate.

The ability of rivastigmine tartrate to improve cognitive performance was assessed with the ADAS-cog.

The ability of rivastigmine tartrate to produce an overall clinical effect was assessed using the Alzheimer’s Disease Cooperative Study – Clinician’s Global Impression of Change (ADCS-CGIC). The ADCS-CGIC is a more standardized form of CIBIC-Plus and is also scored as a 7-point categorical rating, ranging from a score of 1, indicating "markedly improved," to a score of 4, indicating "no change" to a score of 7, indicating "marked worsening".

In this study, 541 patients were randomized to a dose range of 3 mg to 12 mg of rivastigmine tartrate per day or to placebo in a ratio of 2:1, given in divided doses. The 24 week study was divided into a 16 week titration phase and an 8 week maintenance phase. The patients in the active treatment arm of the study were maintained at their highest tolerated dose within the specified dose range.

Figure 7 illustrates the time course for the change from baseline in ADAS-cog scores for both treatment groups over the 24 week study. At 24 weeks of treatment, the mean difference in the ADAS-cog change scores for the rivastigmine tartrate-treated patients compared to the patients on placebo was 3.8 points. This treatment difference was statistically significant in favor of rivastigmine tartrate when compared to placebo.

Figure 7: Time Course of the Change from Baseline in ADAS-cog Score for Patients Completing 24 Weeks of Treatment in Study 4

Figure 8 is a histogram of the distribution of patients’ scores on the ADCS-CGIC (Alzheimer’s Disease Cooperative Study - Clinician’s Global Impression of Change) at 24 weeks. The mean difference in change scores between the rivastigmine tartrate and placebo groups from baseline was 0.5 points. This difference was statistically significant in favor of rivastigmine tartrate treatment.

Figure 8: Distribution of ADCS-CGIC Scores for Patients Completing 24 Weeks of Treatment in Study 4

Patients’ age, gender, or race did not predict clinical outcome of rivastigmine tartrate treatment.

16 HOW SUPPLIED/STORAGE AND HANDLING

Rivastigmine tartrate capsules USP, equivalent to 1.5 mg of rivastigmine base are available as follows:

Rivastigmine tartrate capsules USP, 1.5 mg are white to off-white powder filled in size ‘2’ hard gelatin capsules with light tan opaque color cap and light tan opaque color body, imprinted ‘RDY” on cap and ‘352’ on body with black ink and are supplied in:
Unit dose packages of 100 (10 x 10) NDC 60687-777-01

Store at 20°-25°C (68°-77°F) [see USP Controlled Room Temperature].

FOR YOUR PROTECTION: Do not use if blister is torn or broken.

17 PATIENT COUNSELING INFORMATION

Advice the patient to read the FDA-approved patient labeling

Gastrointestinal Adverse Reactions
Caregivers should be advised of the high incidence of nausea and vomiting associated with the use of the drug along with the possibility of anorexia and weight loss. Caregivers should be encouraged to monitor for these adverse events and inform the physician if they occur. It is critical to inform caregivers that if therapy has been interrupted for more than several days, the next dose should not be administered until they have discussed this with the physician [see Warnings and Precautions (5.1)].

Skin Reactions
Caregivers and patients should be advised that allergic skin reactions have been reported in association with rivastigmine tartrate regardless of formulation (capsules, oral solution or transdermal patch). In case of skin reaction while taking rivastigmine tartrate, patients should consult with their physician immediately [see Warnings and Precautions (5.2)].

Concomitant Use of Drugs with Cholinergic Action
Caregivers and patients should be advised that cholinomimetics, including rivastigmine, may exacerbate or induce extrapyramidal symptoms. Worsening in patients with Parkinson’s disease, including an increased incidence or intensity of tremor, has been observed [see Warnings and Precautions (5.3)].

Pregnancy
Advise patients to notify their healthcare provider if they are pregnant or plan to become pregnant.

Rx Only

PACKAGING INFORMATION

American Health Packaging unit dose blisters (see How Supplied section) contain drug product from Dr. Reddy's Laboratories Limited as follows:
(1.5 mg / 100 UD) NDC 60687-777-01 packaged from NDC 55111-352

Distributed by:
American Health Packaging
Columbus, OH 43217

8477701/0723F

Package/Label Display Panel – Carton – 1.5 mg

NDC 60687- 777-01

Rivastigmine
Tartrate Capsules, USP

1.5 mg*

100 Capsules (10 x 10) Rx Only

*Each Capsule Contains:
Rivastigmine tartrate USP, equivalent to rivastigmine
base 1.5 mg.

Usual Dosage: See package insert for full prescribing
information.

Store at 20° to 25°C (68° to 77°F); excursions permitted
between 15° to 30°C (59° to 86°F) [see USP Controlled
Room Temperature].

Keep this and all drugs out of reach of children.

FOR YOUR PROTECTION: Do not use if blister is torn or
broken.

The drug product contained in this package is from
NDC # 55111-352, Dr. Reddy’s Laboratories Limited.

Distributed by:
American Health Packaging
Columbus, Ohio 43217

777701
0477701/0723

Package/Label Display Panel – Blister – 1.5 mg

Rivastigmine Tartrate
Capsule, USP

1.5 mg